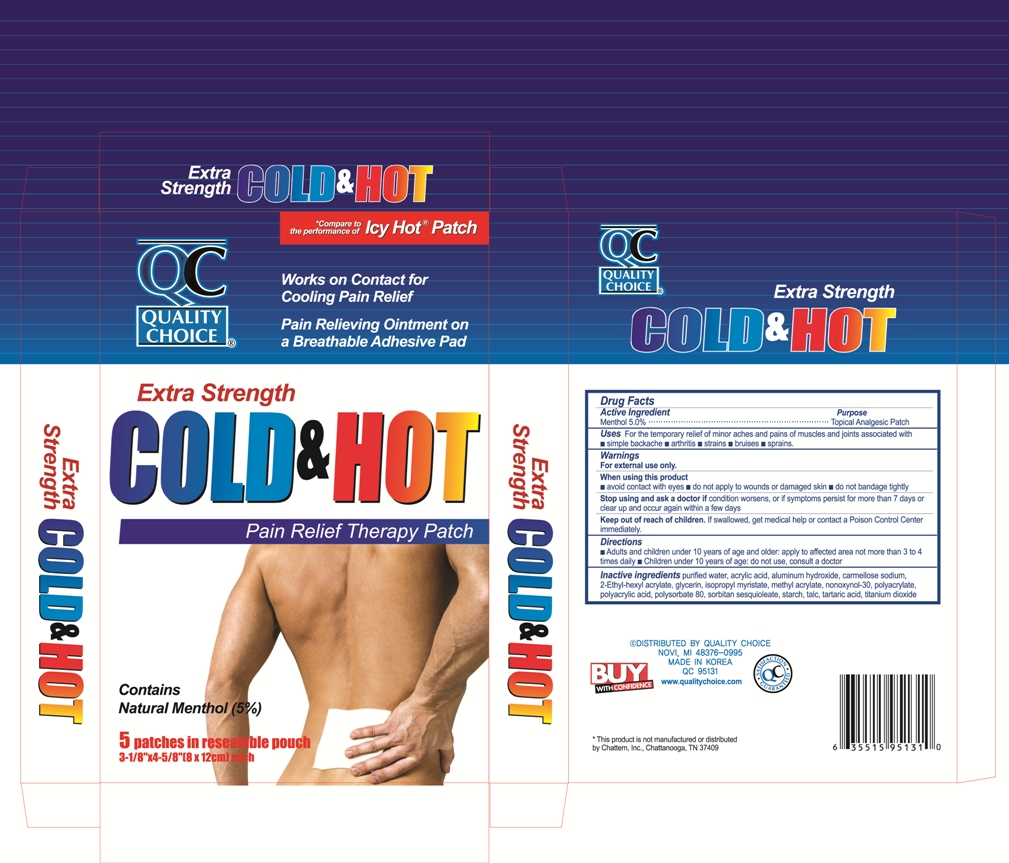 DRUG LABEL: QC Cold and Hot Pain Relief
NDC: 64525-5131 | Form: PATCH
Manufacturer: Quality Home Products
Category: otc | Type: HUMAN OTC DRUG LABEL
Date: 20110912

ACTIVE INGREDIENTS: MENTHOL 400 mg/1 1
INACTIVE INGREDIENTS: WATER; ACRYLIC ACID; ALUMINUM HYDROXIDE; CARBOXYMETHYLCELLULOSE SODIUM; GLYCERIN; ISOPROPYL MYRISTATE; METHYL ACRYLATE; NONOXYNOL-30; POLYSORBATE 80; SORBITAN SESQUIOLEATE; TALC; TARTARIC ACID; TITANIUM DIOXIDE

Drug Facts

Active Ingredient

Menthol 5.0%

Purpose

Topical Analgesic Patch

Uses

For the temporary relief of minor aches and pains of muscles and joints associated with

- simple backache
- arthritis
- strains
- bruises
- sprains

Warnings

For external use only

When using this product

- avoid contact with eyes
- do not apply to wounds or damaged skin
- do not bandage tightly

Stop use and ask a doctor if

condition worsens, or if symptoms persist for more than 7 days or clear up and occur again within a few days

Keep out of reach of children.

If swallowed, get medical help or contact a Poison Control Center right away.

Directions

- Adults and children 10 years of age and older: Apply to affected area not more than 3 to 4 times daily

- Children under 10 years of age: do not use, consult a doctor

Inactive ingredients

Purified Water, Acrylic Acid, Aluminum Hydroxide, Carmellose sodium, 2-Ethylhexyl Acrylate, Glycerin, Isopropyl Myristate, Methyl Acrylate, Nonoxymol-30, Sodium Polyacrylate, Polyacrylic Acid, Polysorbate 80, Sorbitan Sesquioleate, Starch, Talc, Tartaric acid, Titanium Dioxide

package label

QC Cold and Hot Patch